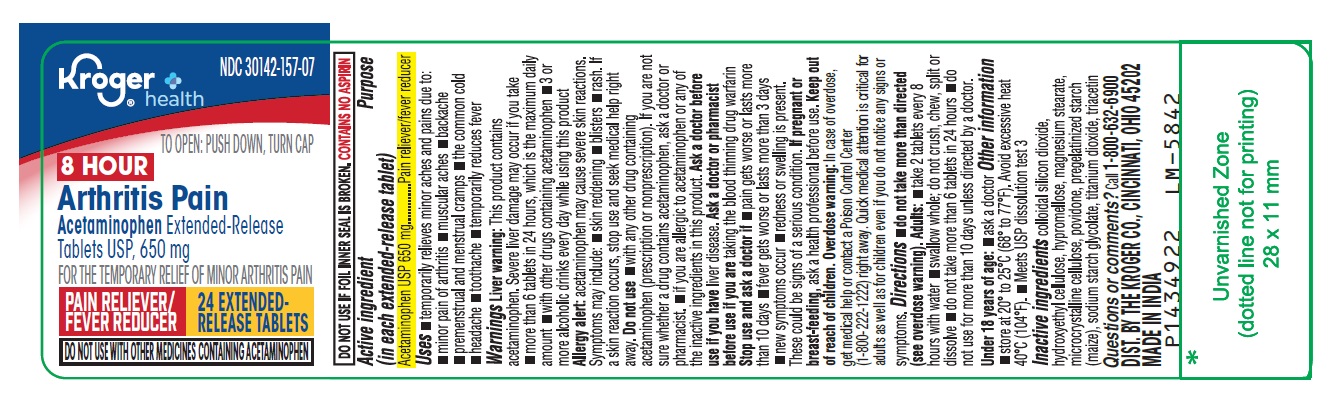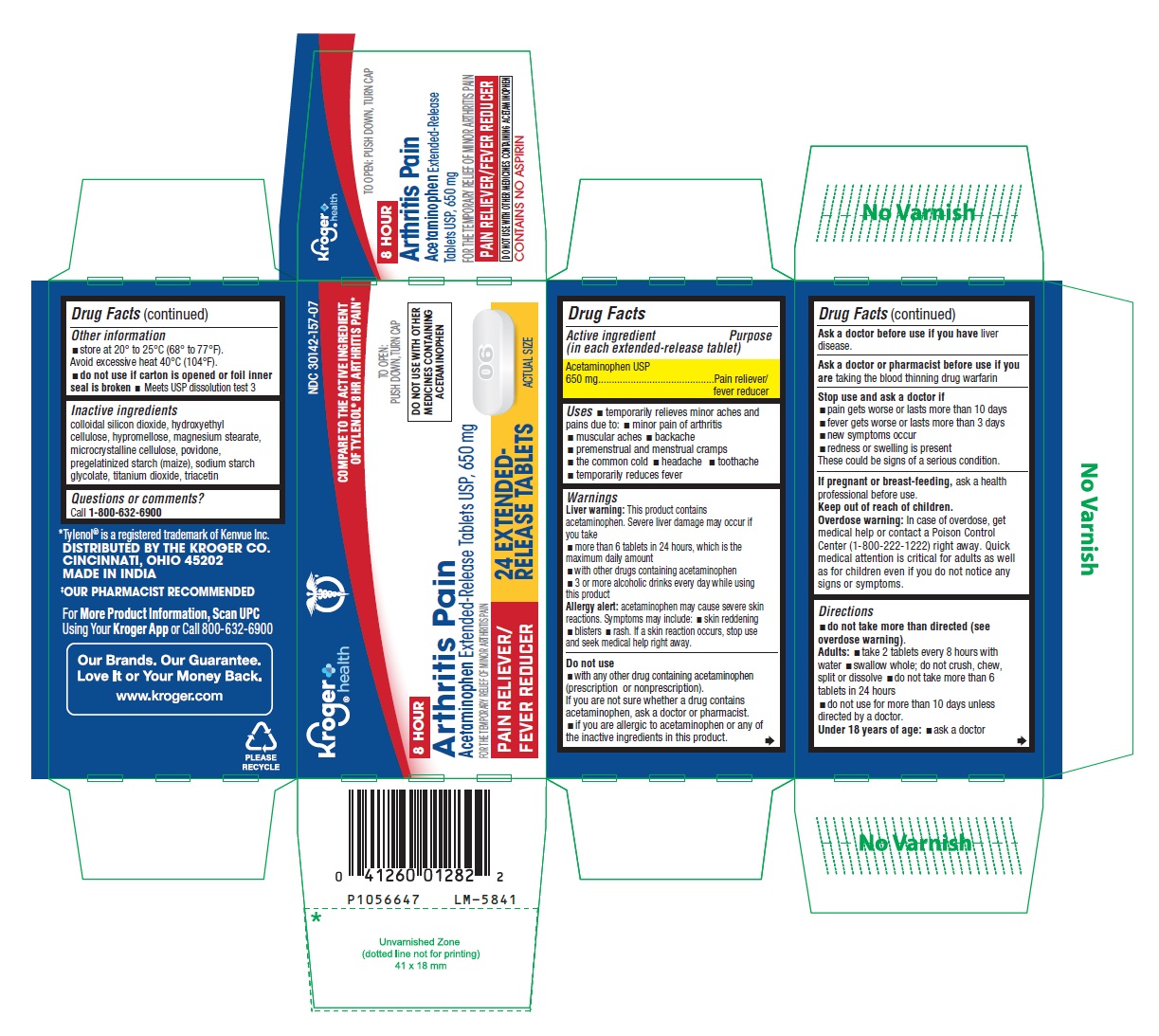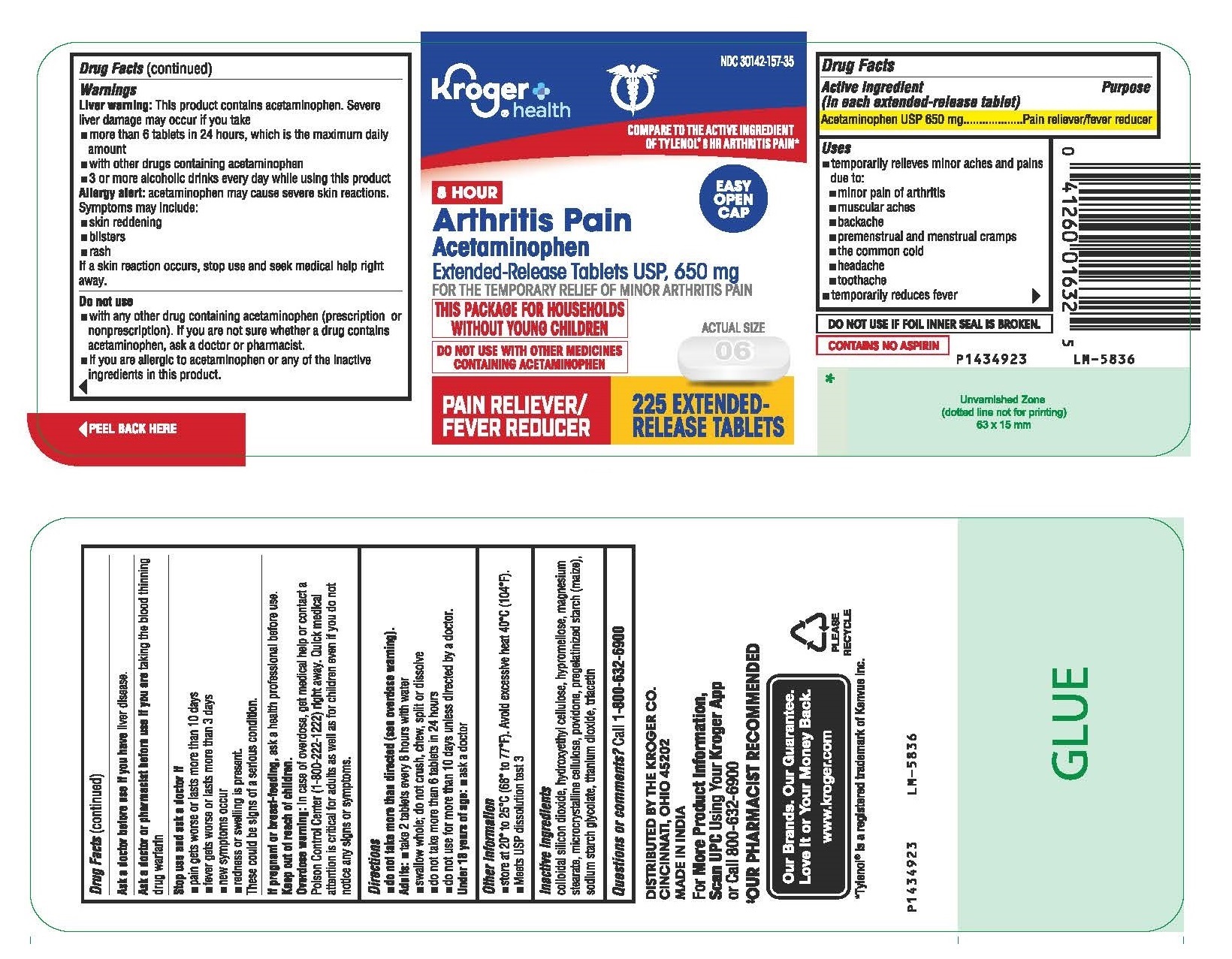 DRUG LABEL: Acetaminophen
NDC: 30142-157 | Form: TABLET, EXTENDED RELEASE
Manufacturer: KROGER COMPANY
Category: otc | Type: Human OTC Drug Label
Date: 20241019

ACTIVE INGREDIENTS: ACETAMINOPHEN 650 mg/1 1
INACTIVE INGREDIENTS: SILICON DIOXIDE; HYDROXYETHYL CELLULOSE (140 MPA.S AT 5%); HYPROMELLOSE, UNSPECIFIED; MAGNESIUM STEARATE; MICROCRYSTALLINE CELLULOSE; POVIDONE, UNSPECIFIED; STARCH, CORN; SODIUM STARCH GLYCOLATE TYPE B POTATO; TITANIUM DIOXIDE; TRIACETIN

Drug Facts

Active ingredient (in each extended-release tablet)
Acetaminophen USP 650 mg

Purpose

Pain reliever/fever reducer

Uses

- temporarily relieves minor aches and pains due to:
  - minor pain of arthritis
  - muscular aches
  - backache
  - premenstrual and menstrual cramps
  - the common cold
  - headache
  - toothache
- temporarily reduces fever

Warnings

Liver warning: This product contains acetaminophen. Severe liver damage may occur if you take

- more than 6 tablets in 24 hours, which is the maximum daily amount
- with other drugs containing acetaminophen
- 3 or more alcoholic drinks every day while using this product

Allergy alert: acetaminophen may cause severe skin reactions. Symptoms may include:

- skin reddening
- blisters
- rash

If a skin reaction occurs, stop use and seek medical help right away.

Do not use

- with any other drug containing acetaminophen (prescription or nonprescription). If you are not sure whether a drug contains acetaminophen, ask a doctor or pharmacist.
- if you are allergic to acetaminophen or any of the inactive ingredients in this product.

Ask a doctor before use if you have liver disease.
Ask a doctor or pharmacist before use if you are taking the blood thinning drug warfarin

Stop use and ask a doctor if

- pain gets worse or lasts more than 10 days
- fever gets worse or lasts more than 3 days
- new symptoms occur
- redness or swelling is present

These could be signs of a serious condition.
If pregnant or breast-feeding, ask a health professional before use.

Keep out of reach of children.

Overdose warning: In case of overdose, get medical help or contact a Poison Control Center right away. (1-800-222-1222) Quick medical attention is critical for adults as well as for children even if you do not notice any signs or symptoms.

Directions

- do not take more than directed (see overdose warning).

Adults:

- take 2 tablets every 8 hours with water
- swallow whole; do not crush, chew, split or dissolve
- do not take more than 6 tablets in 24 hours
- do not use for more than 10 days unless directed by a doctor.

Under 18 years of age:

- ask a doctor

Other information

- store at 20o to 25oC (68o to 77oF). Avoid excessive heat 40oC (104oF).
- do not use if carton is opened or foil inner seal is broken
- Meets USP dissolution test 3

Inactive ingredients

colloidal silicon dioxide, hydroxyethyl cellulose, hypromellose, magnesium stearate, microcrystalline cellulose, povidone, pregelatinized starch (maize), sodium starch glycolate, titanium dioxide, triacetin
Questions or comments?
1-800-632-6900
DISTRIBUTED BY THE KROGER CO.
CINCINNATI, OHIO 45202
MADE IN INDIA
Code: TS/DRUGS/22/2009

PACKAGE LABEL-PRINCIPAL DISPLAY PANEL - 650 mg (24 Tablet Container Label)

NDC 30142-157-07
Kroger®
health
TO OPEN: PUSH DOWN, TURN CAP
8 HOUR
Arthritis Pain
Acetaminophen Extended-Release
Tablets USP, 650 mg
FOR THE TEMPORARY RELIEF OF MINOR ARTHRITIS PAIN
PAIN RELIEVER/ 24 EXTENDED-
FEVER REDUCER RELEASE TABLETS
DO NOT USE WITH OTHER MEDICINES CONTAINING ACETAMINOPHEN

PACKAGE LABEL-PRINCIPAL DISPLAY PANEL - 650 mg (24 Tablets Container Carton)

NDC 30142-157-07
COMPARE TO THE ACTIVE INGREDIENT
OF TYLENOL® 8HR ARTHRITIS PAIN *
Kroger®
health
TO OPEN:
PUSH DOWN, TURN CAP
DO NOT USE WITH OTHER
MEDICINES CONTAINING
ACETAMINOPHEN
8 HOUR
Arthritis Pain
Acetaminophen Extended-Release Tablets USP, 650 mg
FOR THE TEMPORARY RELIEF OF MINOR ARTHRITIS PAIN
PAIN RELIEVER/ 24 EXTENDED-
FEVER REDUCER RELEASE TABLETS
ACTUAL SIZE

PACKAGE LABEL-PRINCIPAL DISPLAY PANEL - 650 mg (225 Tablet Container Label)

NDC 30142-157-35
Kroger®
health
COMPARE TO THE ACTIVE INGREDIENT
OF TYLENOL® 8HR ARTHRITIS PAIN *

EASY
OPEN
CAP

8 HOUR
Arthritis Pain
Acetaminophen
Extended-Release Tablets USP, 650 mg
FOR THE TEMPORARY RELIEF OF MINOR ARTHRITIS PAIN
THIS PACKAGE FOR HOUSEHOLDS
WITHOUT YOUNG CHILDERN
DO NOT USE WITH OTHER MEDICINES ACTUAL SIZE
CONTAINING ACETAMINOPHEN
PAIN RELIEVER/ 225 EXTENDED-
FEVER REDUCER RELEASE TABLETS